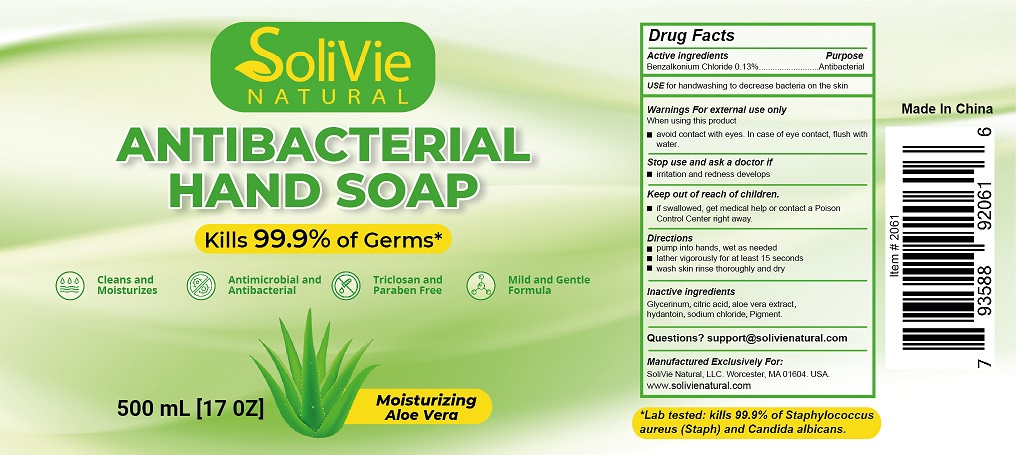 DRUG LABEL: Solivie Natural Antibacterial Hand
NDC: 75183-112 | Form: SOAP
Manufacturer: Zorin Pharmaceutical Technology (Hangzhou) Co Ltd.
Category: otc | Type: HUMAN OTC DRUG LABEL
Date: 20210224

ACTIVE INGREDIENTS: BENZALKONIUM CHLORIDE 1.3 mg/1 mL
INACTIVE INGREDIENTS: WATER; GLYCERIN; HYDANTOIN; SODIUM CHLORIDE

Active ingredient

Benzalkonium Chloride ................. 0.13%

Purpose

Antibacterial

USE

For handwashing to decrease bacteria on the skin.

Warnings

For external use only.

When using this product

- avoid contact with eyes. In case of eye contact, flush with water.

Stop use and ask a doctor

if irritation and redness develops.

Keep out of reach of children.

If swallowed, get medical help or contact a Poison Control Center right away.

Directions

- pump into hands, wet as needed
- lather vigorously for at least 15 seconds
- wash skin rinse thoroughly and dry

Inactive ingredients

Glycerin, Citric Acid, aloe vera extract, hydantoin, sodium chloride, pigment